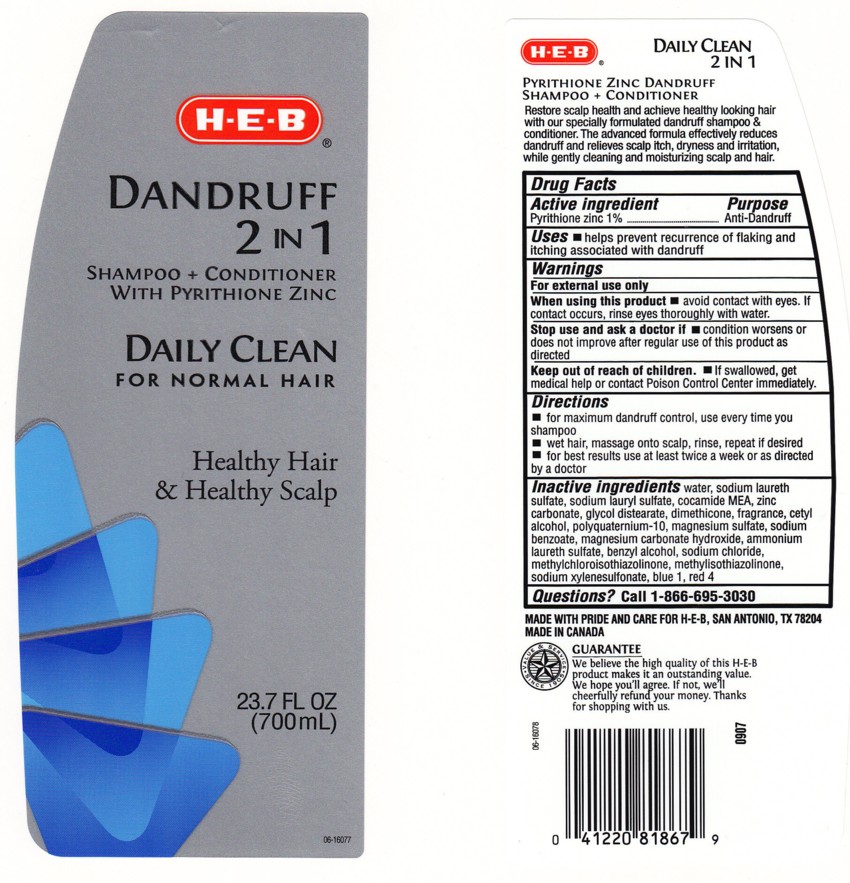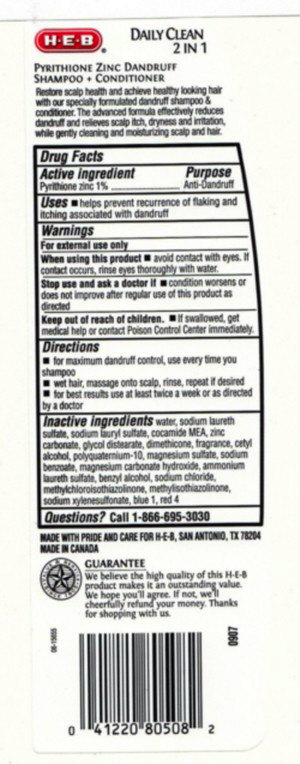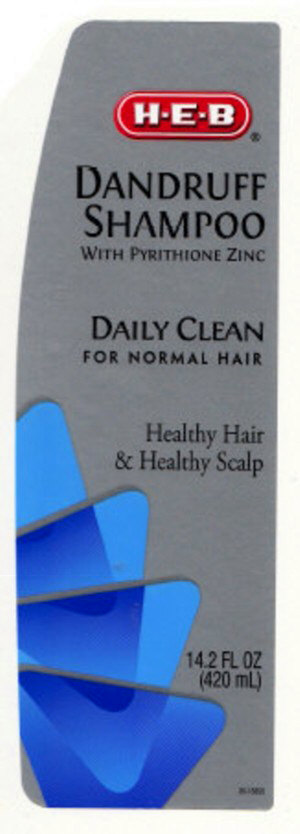 DRUG LABEL: DANDRUFF 2 IN 1 SHAMPOO AND CONDITIONER 
NDC: 37808-415 | Form: LOTION/SHAMPOO
Manufacturer: HEB
Category: otc | Type: HUMAN OTC DRUG LABEL
Date: 20100308

ACTIVE INGREDIENTS: PYRITHIONE ZINC 1.0000 mL/100 mL

Dandruff Shampoo and Conditioner

ACTIVE INGREDIENT

PYRITHIONE ZINC 1% (ANTI - DANDRUFF)

USES

HELPS PREVENT RECURRENCE OF FLAKING AND ITCHING ASSOCIATED WITH DANDRUFF

WARNINGS

FOR EXTERNAL USE ONLY

WHEN USING THIS PRODUCT

AVOID CONTACT WITH EYES. IF CONTACT OCCURS, RINSE EYES THROUGHLY WITH WATER.

STOP USE AND ASK A DOCTOR IF

CONDITION WORSENS OR DOES NOT IMPROVE AFTER REGULAR USE OF THIS PRODUCT AS DIRECTED

KEEP OUT OF REACH OF CHILDREN

IF SWALLOWED, GET MEDICAL HELP OR CONTACT POISON CONTROL CENTER IMMEDIATELY.

QUESTIONS?

CALL 1-866-695-3030

Package Front and Back Labels

- 14OZ Front Label: hebf14.jpg
- 14OZ Back Label: hebb14.jpg
- 24OZ FRONT AND BACK LABELS: heb24.jpg